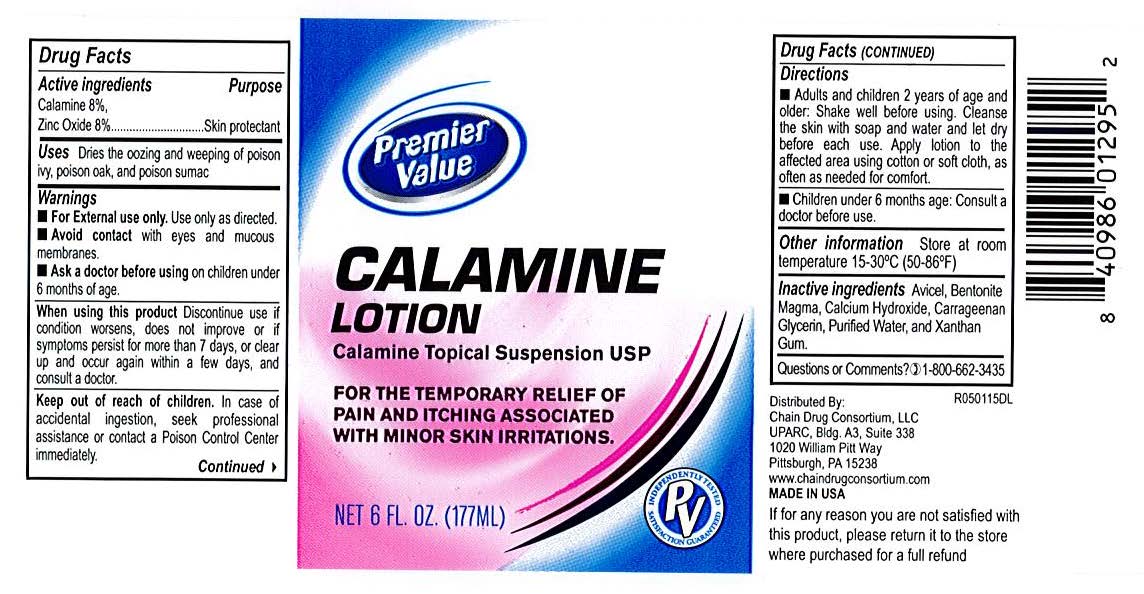 DRUG LABEL: Premiere Value Calamine
NDC: 68016-413 | Form: LOTION
Manufacturer: Chain Drug Consortium
Category: otc | Type: HUMAN OTC DRUG LABEL
Date: 20231220

ACTIVE INGREDIENTS: ZINC OXIDE 160 mg/1 mL
INACTIVE INGREDIENTS: BENTONITE; CALCIUM HYDRIDE; GLYCERIN; WATER

Premiere Value Calamine Lotion

Drug Facts

active Ingredients

Calamine 8%

Zinc Oxide 8%

Purpose

Skin Protectant

Skin Protectant

Uses

Dries the oozing and weeping of poison ivy, poison oak, and poison sumac and other skin irritations.

Warnings

For external use only. Use only as directed.

Avoid contat with eyes and moucous membranes.

Ask a doctor

before using on children under 6 years of age.

Stop use and ask a doctor if

- Condition worsens
- Symptoms last for more than 7 days or clear up and occur again within a few days.

Keep out of reach of children.

In case of accidental ingestion, seek professional assistance or contact a Poison Control Center immediately.

Directions

Adults and children 6 mo. of age and older: Shake well before using. Cleanse the skin with soap and water. Let dry before each use. Apply lotion to the affected area using cotton or soft cloth, as often as needed for comfort.

Children under 6 mo. of age: Consult a doctor before use.

Other information

Store at room temperature 15-30C (59-86F)

Inactive Ingredients

Bentonite Magma, Calcium Hydroxide, Glycerin, and Purified Water.